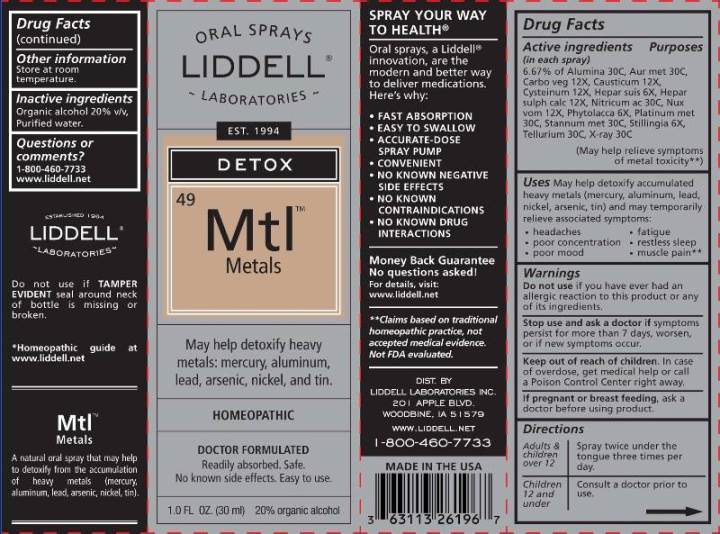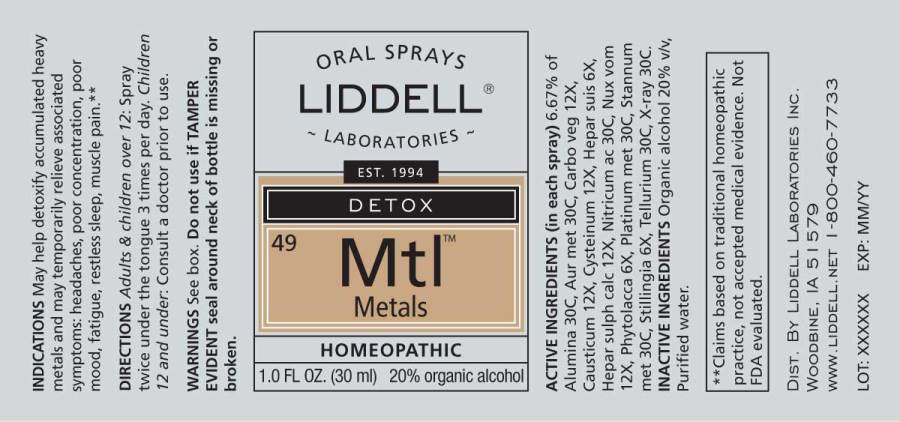 DRUG LABEL: Metals
NDC: 50845-0249 | Form: SPRAY
Manufacturer: Liddell Laboratories, Inc.
Category: homeopathic | Type: HUMAN OTC DRUG LABEL
Date: 20240701

ACTIVE INGREDIENTS: ALUMINUM OXIDE 30 [hp_C]/1 mL; GOLD 30 [hp_C]/1 mL; ACTIVATED CHARCOAL 12 [hp_X]/1 mL; CAUSTICUM 12 [hp_X]/1 mL; CYSTEINE 12 [hp_X]/1 mL; PORK LIVER 6 [hp_X]/1 mL; CALCIUM SULFIDE 12 [hp_X]/1 mL; NITRIC ACID 30 [hp_C]/1 mL; STRYCHNOS NUX-VOMICA SEED 12 [hp_X]/1 mL; PHYTOLACCA AMERICANA ROOT 6 [hp_X]/1 mL; PLATINUM 30 [hp_C]/1 mL; TIN 30 [hp_C]/1 mL; STILLINGIA SYLVATICA ROOT 6 [hp_X]/1 mL; TELLURIUM 30 [hp_C]/1 mL; ALCOHOL, X-RAY EXPOSED (1000 RAD) 30 [hp_C]/1 mL
INACTIVE INGREDIENTS: WATER; ALCOHOL

DRUG FACTS:

ACTIVE INGREDIENTS:

(in each spray): 6.67% Alumina 30C, Aurum metallicum 30C, Carbo vegetabilis 12X, Causticum 12X, Cysteinum 12X, Hepar suis 6X, Hepar sulphuris calcareum 12X, Nitricum acidum 30C, Nux vomica 12X, Phytolacca decandra 6X, Platinum metallicum 30C, Stannum metallicum 30C, Stillingia sylvatica 6X, Tellurium metallicum 30C, X-Ray 30C.

USES:

May help detoxify accumulated heavy metals (mercury, aluminum, lead, nickel, arsenic, tin) and may temporarily relieve associated symptoms:

• headaches

• poor concentration

• poor mood

• fatigue

• restless sleep

• muscle pain**

**Claims based on traditional homeopathic practice, not accepted medical evidence. Not FDA evaluated.

WARNINGS:

Do not use if you have ever had an allergic reaction to this product or any of its ingredients.

Stop use and ask a doctor if symptoms persist for more than 7 days, worsen or if new symptoms occur.

Keep out of reach of children. In case of overdose, get medical help or call a Poison Control Center right away.

If pregnant or breast feeding, ask a doctor before using product.

Store at room temperature.

Do not use if TAMPER EVIDENT seal around neck of bottle is missing or broken.

Keep out of reach of children. In case of overdose, get medical help or call a Poison Control Center right away.

DIRECTIONS:

Children 12 and under: Consult a doctor prior to use.

Adults & children over 12: Spray twice under the tongue three times per day.

For heavy exposure to toxic metals such as mercury, aluminum, and tin in dental amalgam fillings, or other toxic metals use daily for first month, then daily every other week. For light exposure, use daily the first month, then daily one week per month for the next three months.

INDICATIONS:

May help detoxify accumulated heavy metals (mercury, aluminum, lead, nickel, arsenic, tin) and may temporarily relieve associated symptoms:

• headaches

• poor concentration

• poor mood

• fatigue

• restless sleep

• muscle pain**

**Claims based on traditional homeopathic practice, not accepted medical evidence. Not FDA evaluated.

INACTIVE INGREDIENTS:

Organic alcohol 20% v/v, Purified water

QUESTIONS:

DIST. BY

LIDDELL LABORATORIES INC.

201 APPLE BLVD

WWW.LIDDELL.NET

1-800-460-7733

PACKAGE LABEL DISPLAY:

ORAL SPRAYS
LIDDELL
LABORATORIES
EST 1994
DETOX
^49 Mtl
Metals
May help detoxify heavy
metals: mercury, aluminum,
lead, arsenic, nickel, and tin.
HOMEOPATHIC

DOCTOR FORMULATED
Readily absorbed. Safe.
No known side effects. Easy to use.
1.0 FL OZ (30 ml)